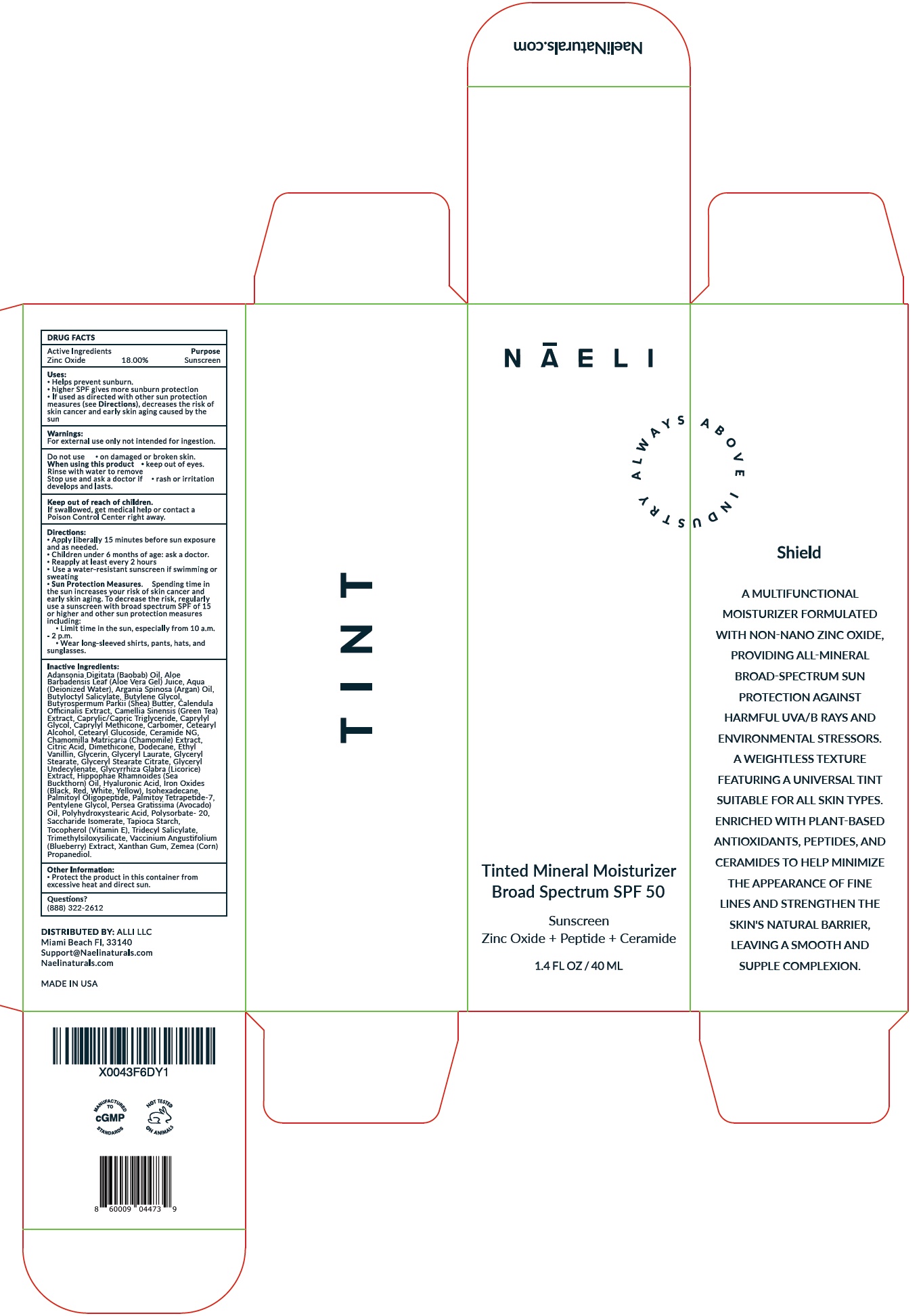 DRUG LABEL: NAELI TINT Tinted Mineral Moisturizer SPF 50
NDC: 73670-549 | Form: CREAM
Manufacturer: ALLI LLC
Category: otc | Type: HUMAN OTC DRUG LABEL
Date: 20240327

ACTIVE INGREDIENTS: ZINC OXIDE 180 mg/1 mL
INACTIVE INGREDIENTS: ALOE VERA LEAF; WATER; BUTYLOCTYL SALICYLATE; BUTYLENE GLYCOL; SHEA BUTTER; CALENDULA OFFICINALIS FLOWER; GREEN TEA LEAF; MEDIUM-CHAIN TRIGLYCERIDES; CAPRYLYL GLYCOL; CAPRYLYL TRISILOXANE; CARBOMER HOMOPOLYMER, UNSPECIFIED TYPE; CETOSTEARYL ALCOHOL; CETEARYL GLUCOSIDE; CERAMIDE NG; CHAMOMILE; CITRIC ACID MONOHYDRATE; DIMETHICONE; DODECANE; ETHYL VANILLIN; GLYCERIN; GLYCERYL LAURATE; GLYCERYL MONOSTEARATE; GLYCERYL STEARATE CITRATE; LICORICE; HYALURONIC ACID; FERRIC OXIDE RED; ISOHEXADECANE; PALMITOYL TRIPEPTIDE-1; PALMITOYL TETRAPEPTIDE-7; PENTYLENE GLYCOL; AVOCADO OIL; SACCHARIDE ISOMERATE; STARCH, TAPIOCA; .ALPHA.-TOCOPHEROL; TRIDECYL SALICYLATE; BLUEBERRY; XANTHAN GUM; CORN

NAELI TINT Tinted Mineral Moisturizer SPF-50

Active Ingredients

Zinc Oxide 18.00%

Purpose

Sunscreen

Uses:

- Helps prevent sunburn.
- higher SPF gives more sunburn protection
- If used as directed with other sun protection measures (see Directions), decreases the risk of skin cancer and early skin aging caused by the sun

Warnings:

For external use only not intented for ingestion.

Do not use

- on damaged or broken skin.

When using this product

- keep out of eyes.

Rinse with water to remove

Stop use and ask a doctor if

- rash or irritation develops and lasts.

Keep out of reach of children.

If swallowed, get medical help or contact a Poison Control Center right away.

Directions:

- Apply liberally 15 minutes before sun exposure and as needed.
- Children under 6 months of age: ask a doctor.
- Reapply at least every 2 hours
- Use a water-resistant sunscreen if swimming or sweating
- Sun Protection Measures.Spending time in the sun increases your risk of skin cancer and early skin aging. To decrease the risk, regularly use a sunscreen with broad spectrum SPF of 15 or higher and other sun protection measures including:
- Limit time in the sun, especially from 10 a.m.-2 p.m.
- Wear long-sleeved shirts, pants, hats, and sunglasses.

Inactive Ingredients:

Adansonia Digitata (Baobab) Oil, Aloe Barbadensis Leaf (Aloe Vera Gel) Juice, Aqua (Deionized Water), Argania Spinosa (Argan) Oil, Butyloctyl Salicylate, Butylene Glycol, Butyrospermum Parkii (Shea) Butter, Calendula Officinalis Extract, Camellia S inensis (Green Tea) Extract, Caprylic/Capric Triglyceride, Caprylyl Glycol, Caprylyl Methicone, Carbomer, Cetearyl Alcohol, Cetearyl Glucoside, Ceramide NG, Chamomilla Matricaria (Chamomile) Extract, Citric Acid, Dimethicone, Dodecane, Ethyl Vanillin, Glycerin, Glyceryl Laurate, Glyceryl
Stearate, Glyceryl Stearate Citrate, Glyceryl Undecylenate, Glycyrrhiza Glabra (Licorice) Extract, Hippophae Rhamnoides (Sea Buckthorn) Oil, Hyaluronic Acid, Iron Oxides (Black, Red, White, Yellow), Isohexadecane, Palmitoyl Oligopeptide, Palmitoy Tetrapetide-7, Pentylene Glycol, Persea Gratissima (Avocado) Oil, Polyhydroxystearic Acid, Polysorbate- 20, Saccharide Isomerate, Tapioca Starch, Tocopherol (Vitamin E), Tridecyl Salicylate, Trimethylsiloxysilicate, Vaccinium Angustifolium (Blueberry) Extract, Xanthan Gum, Zemea (Corn) Propanediol.

Other Information:

- Protect the product in this container from excessive heat and direct sun.

Questions?

(888) 322-2612